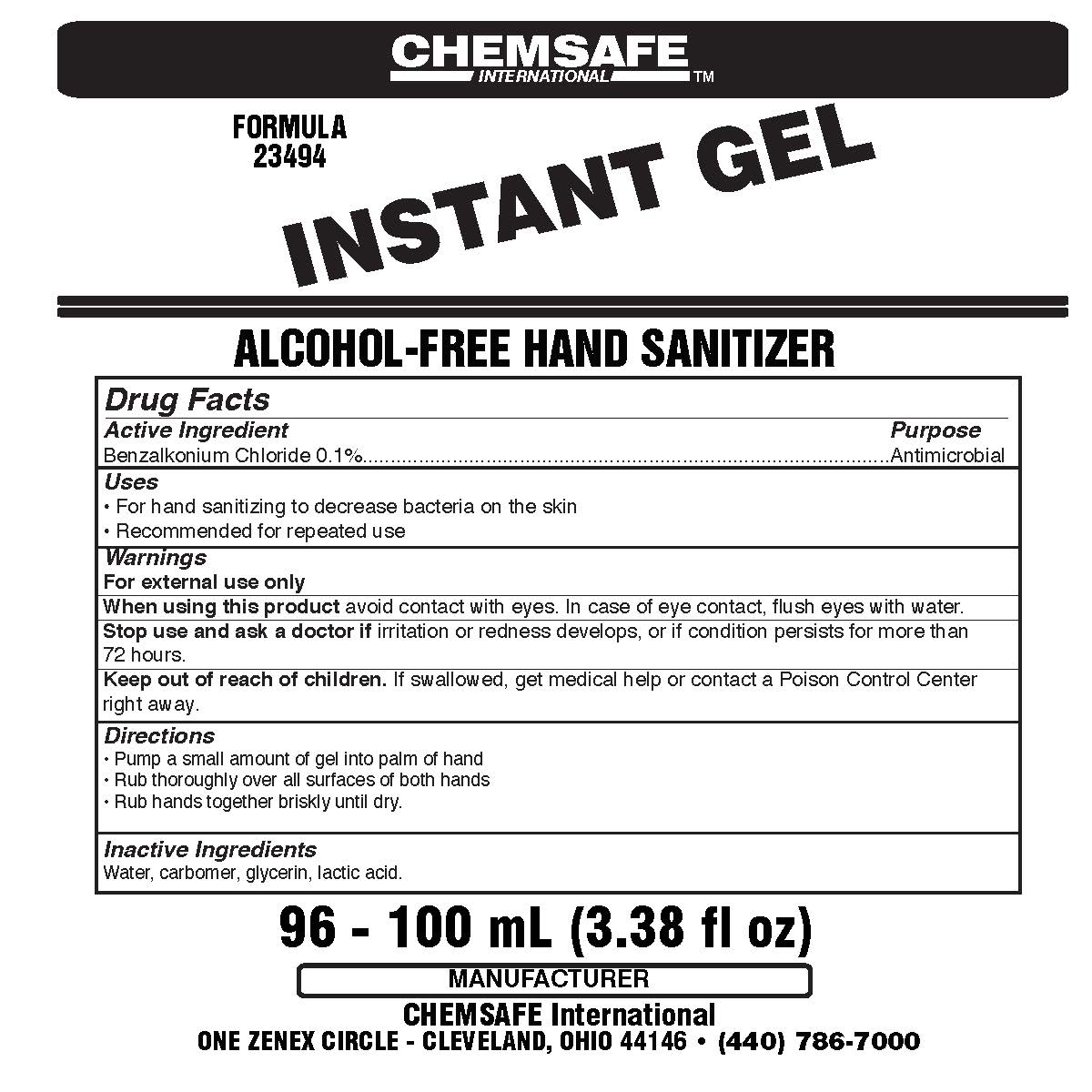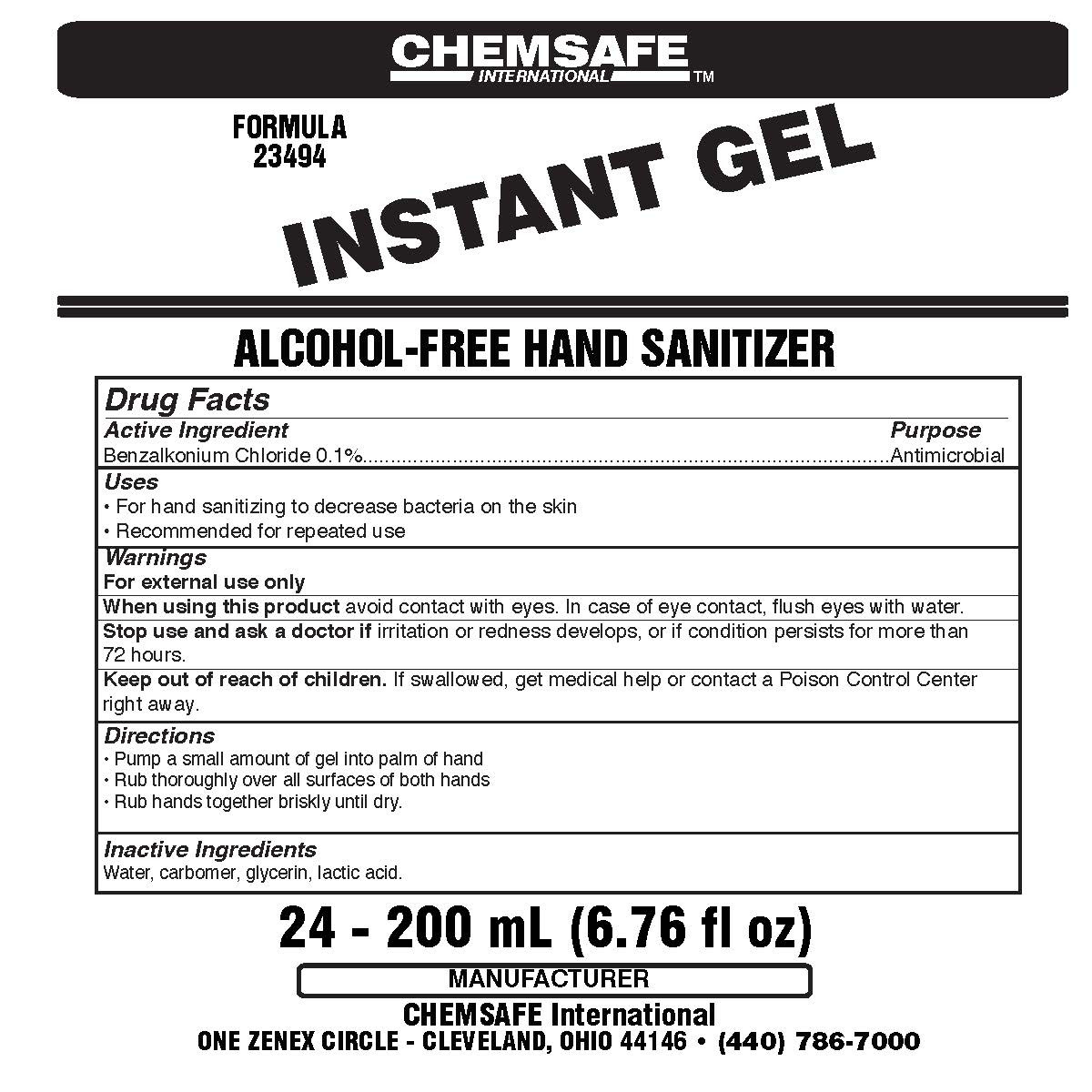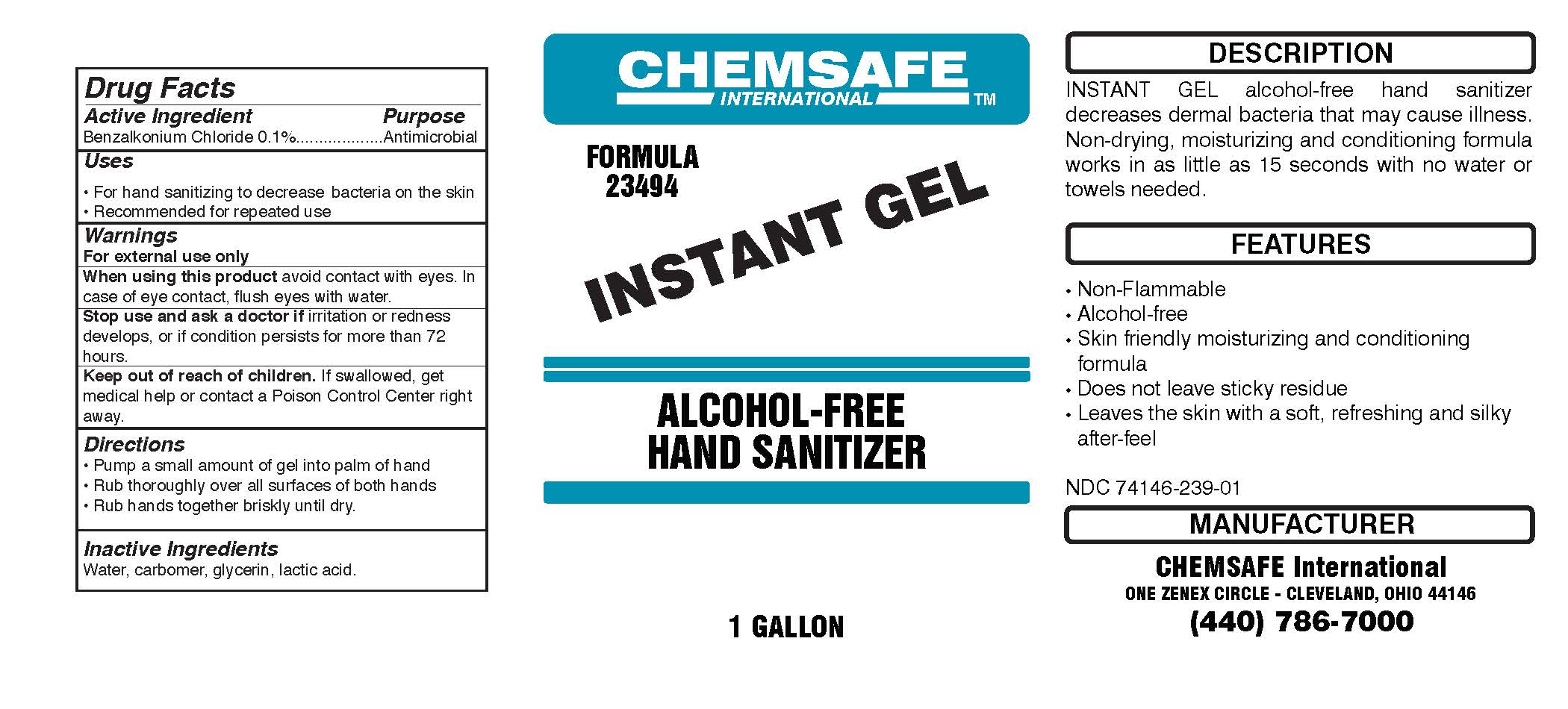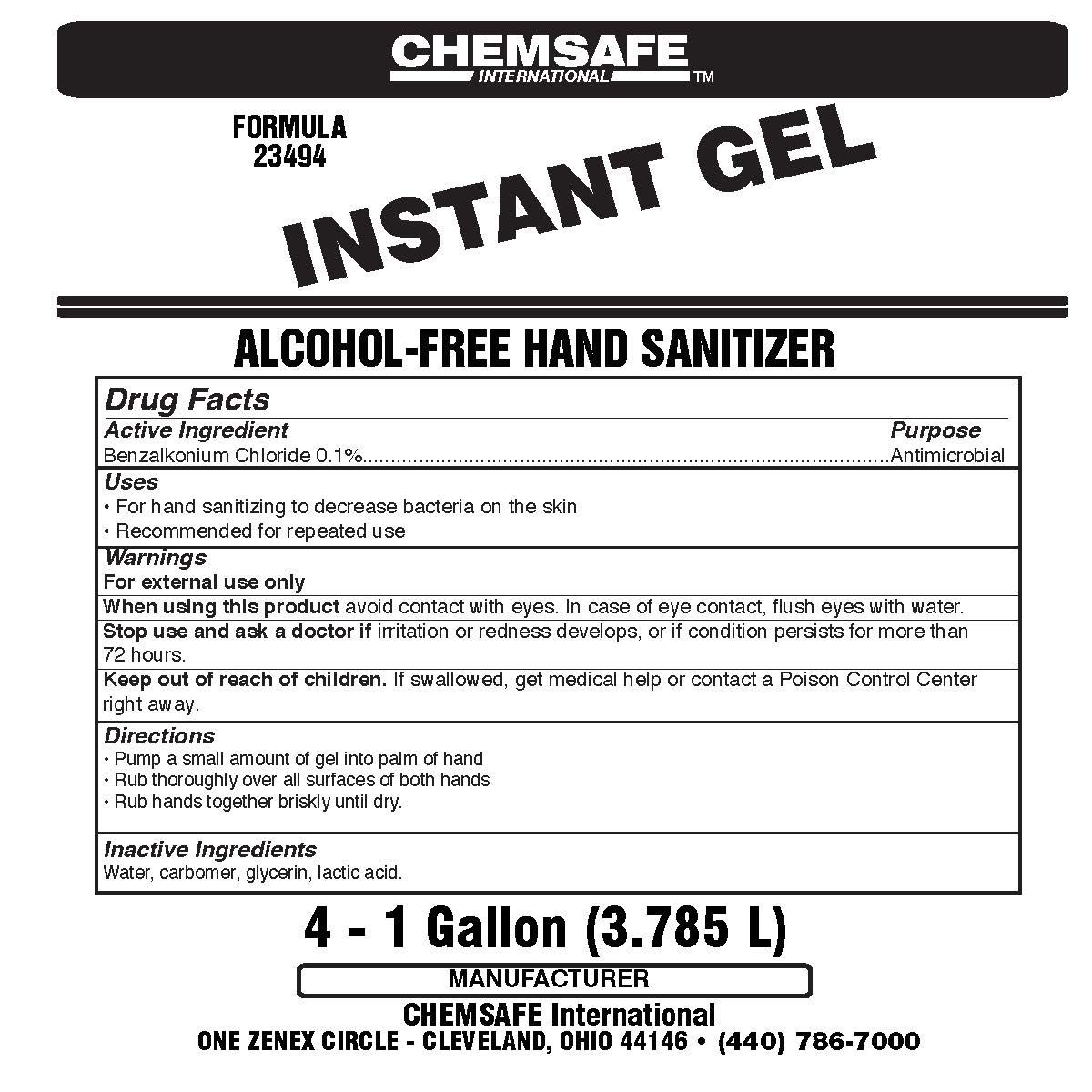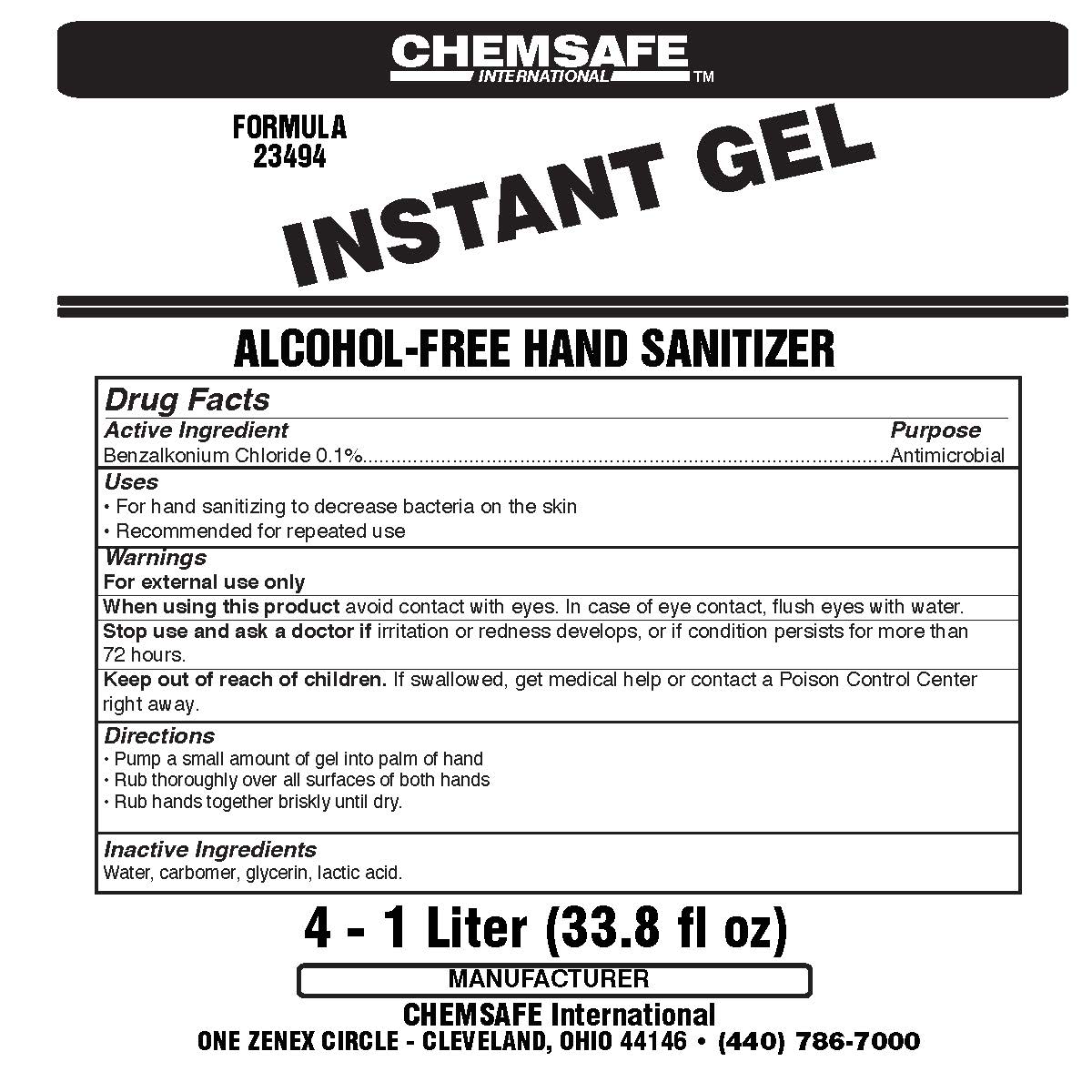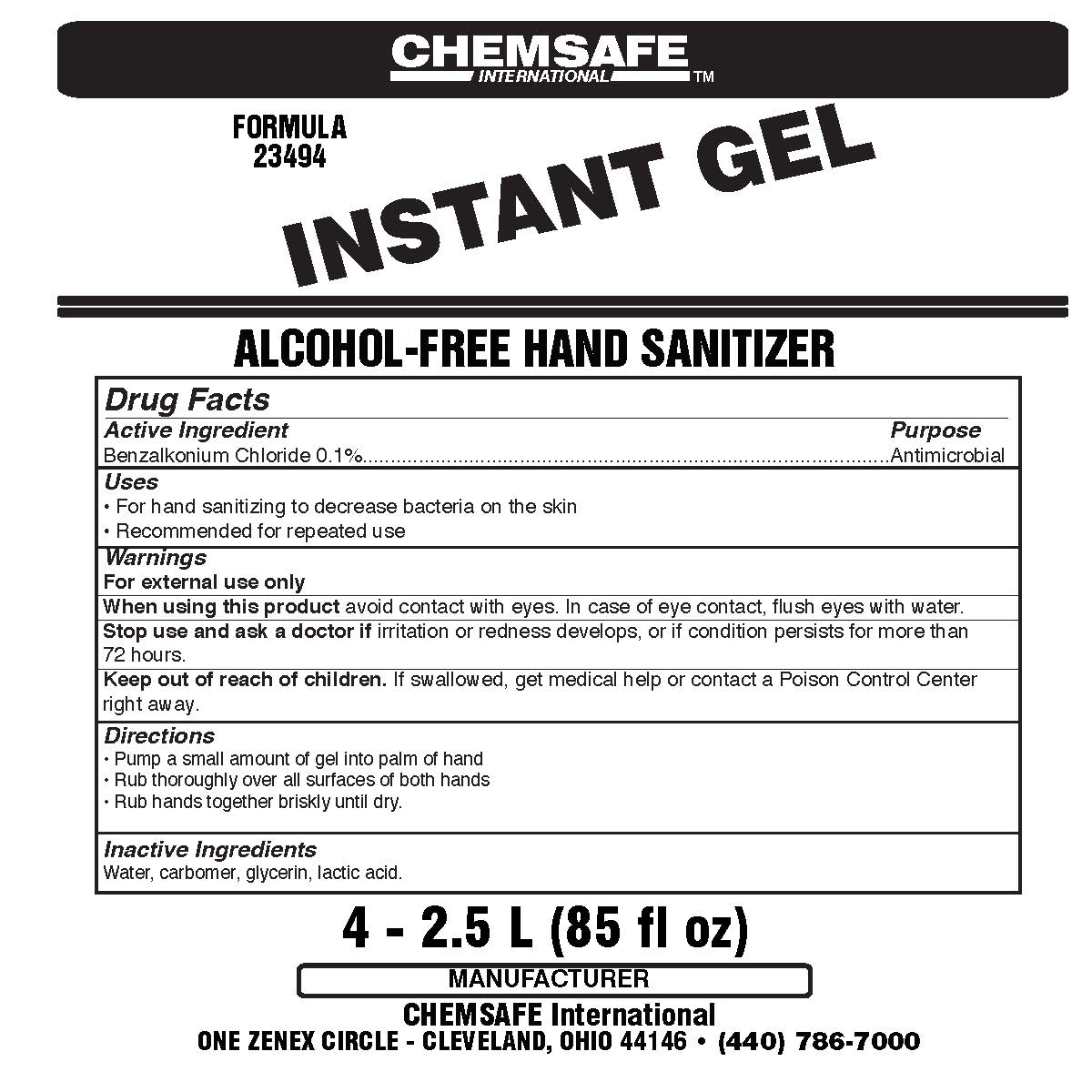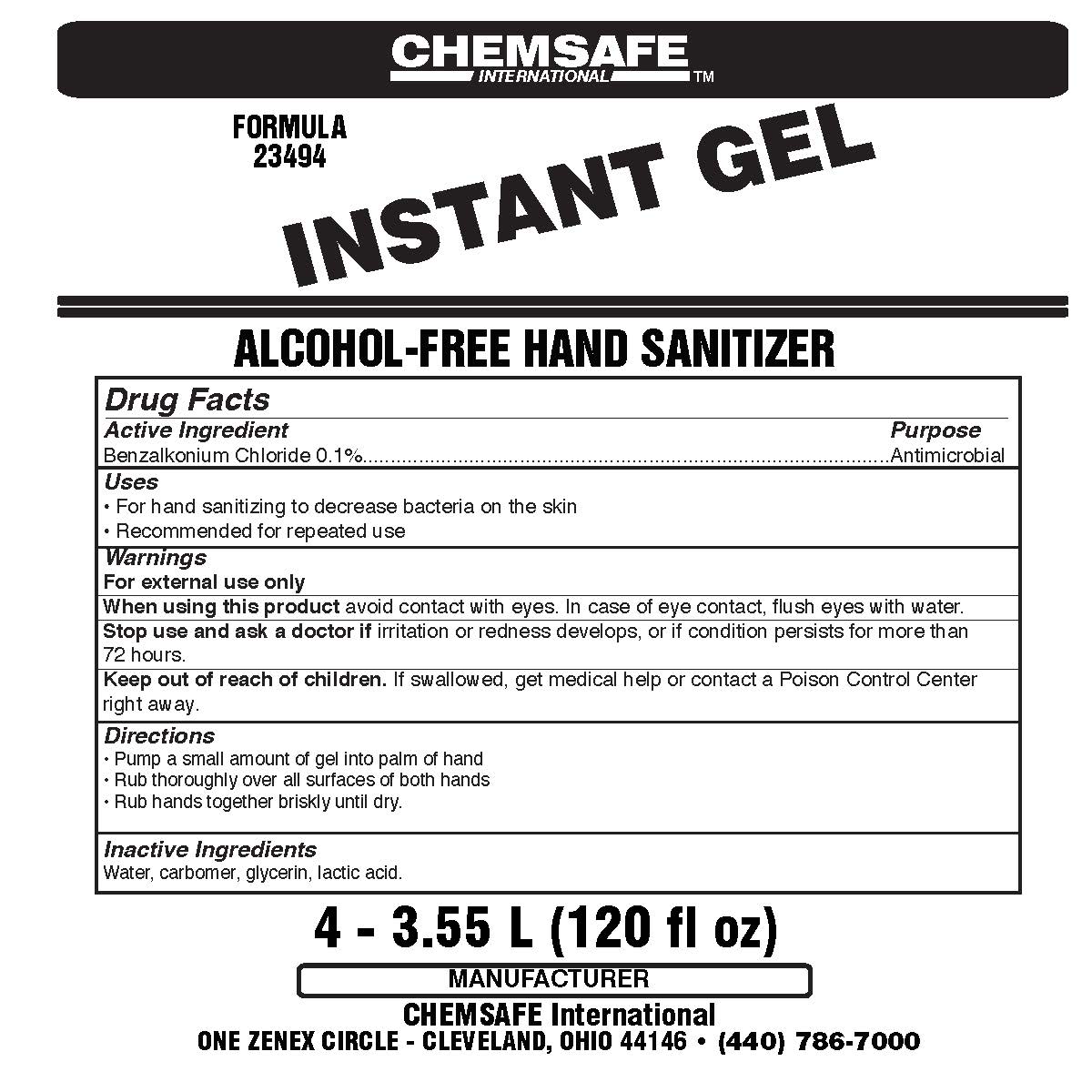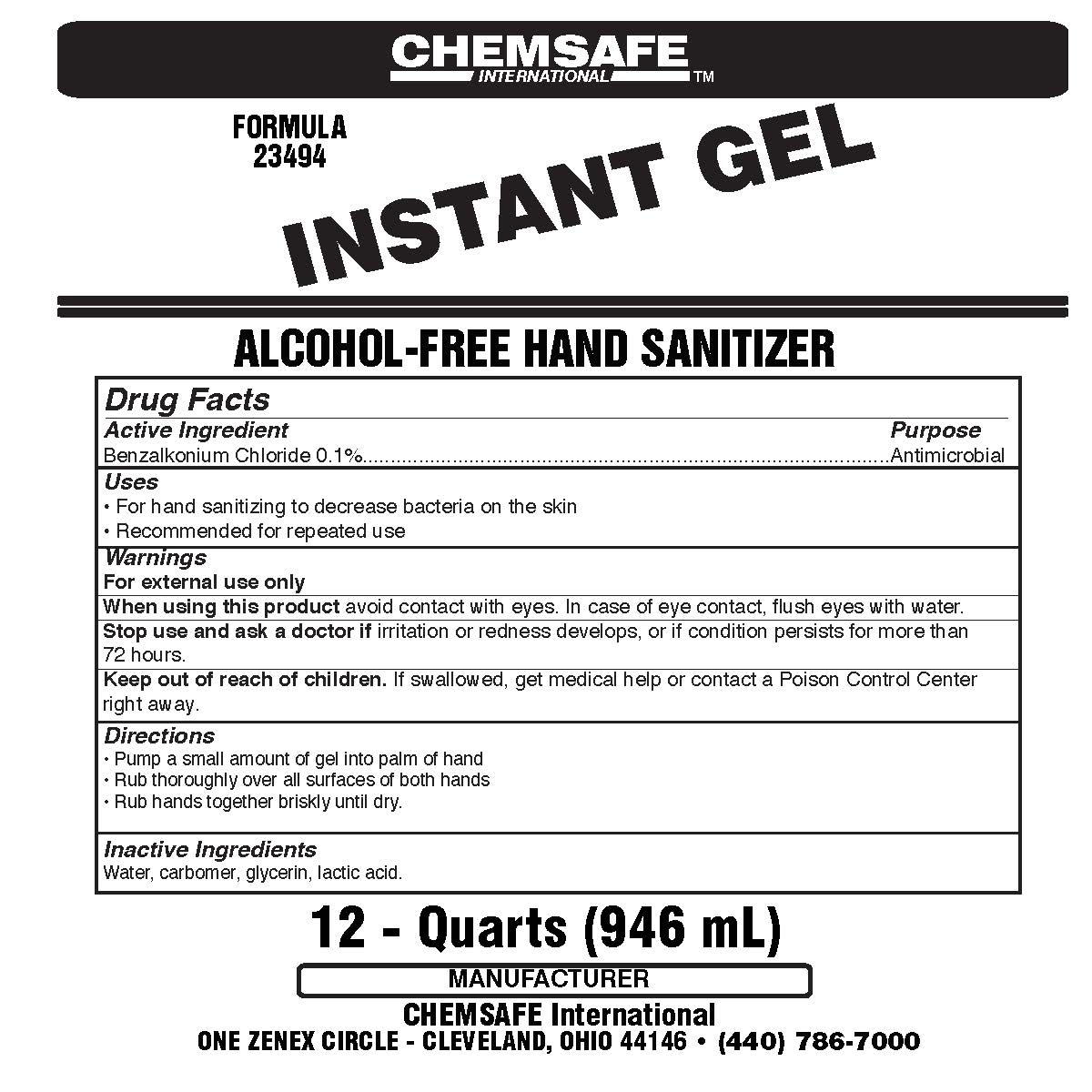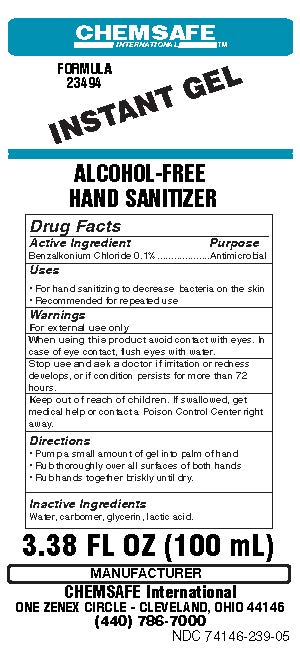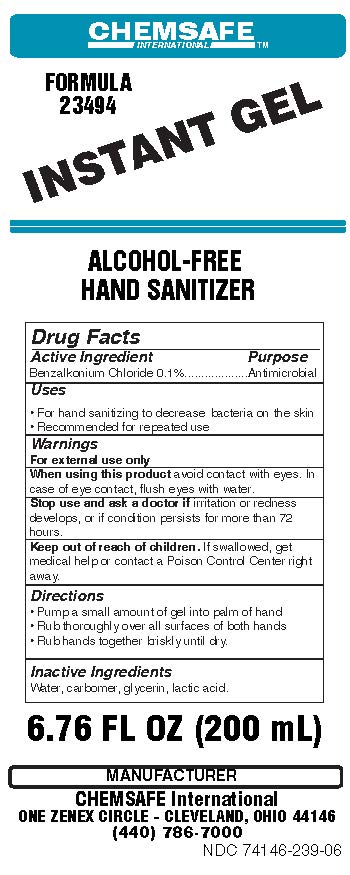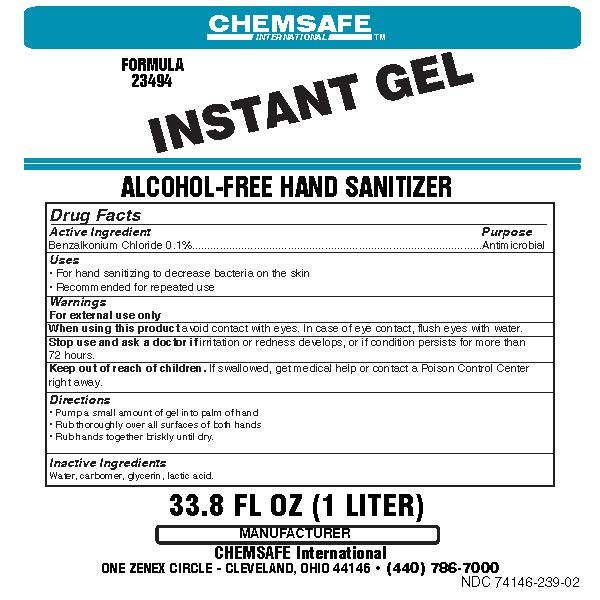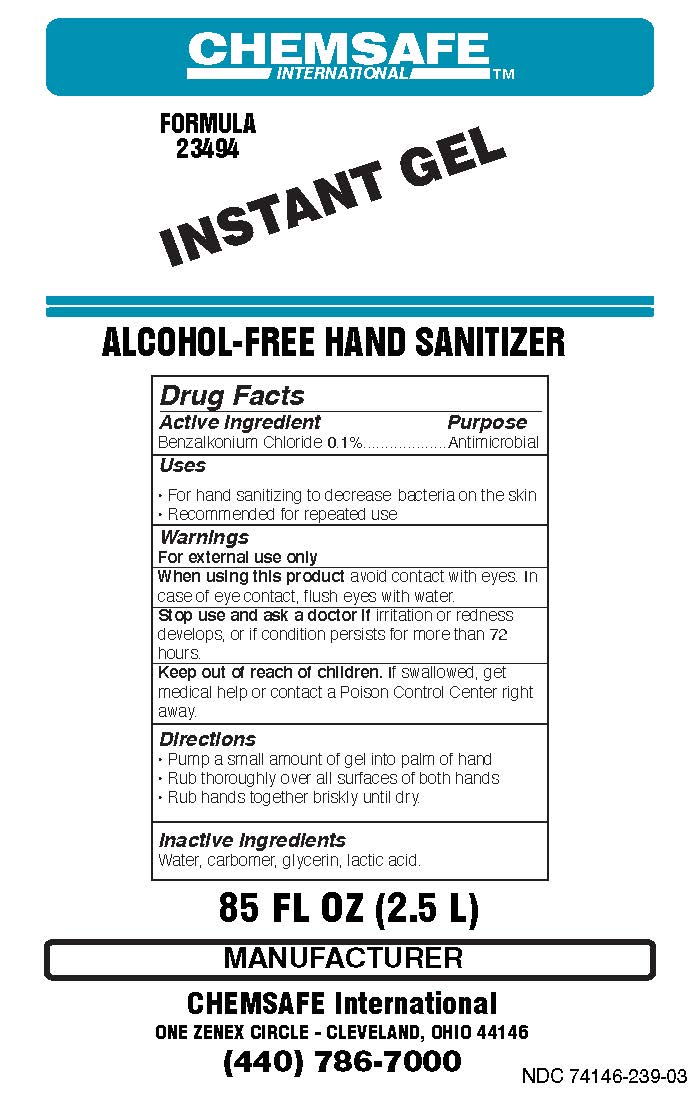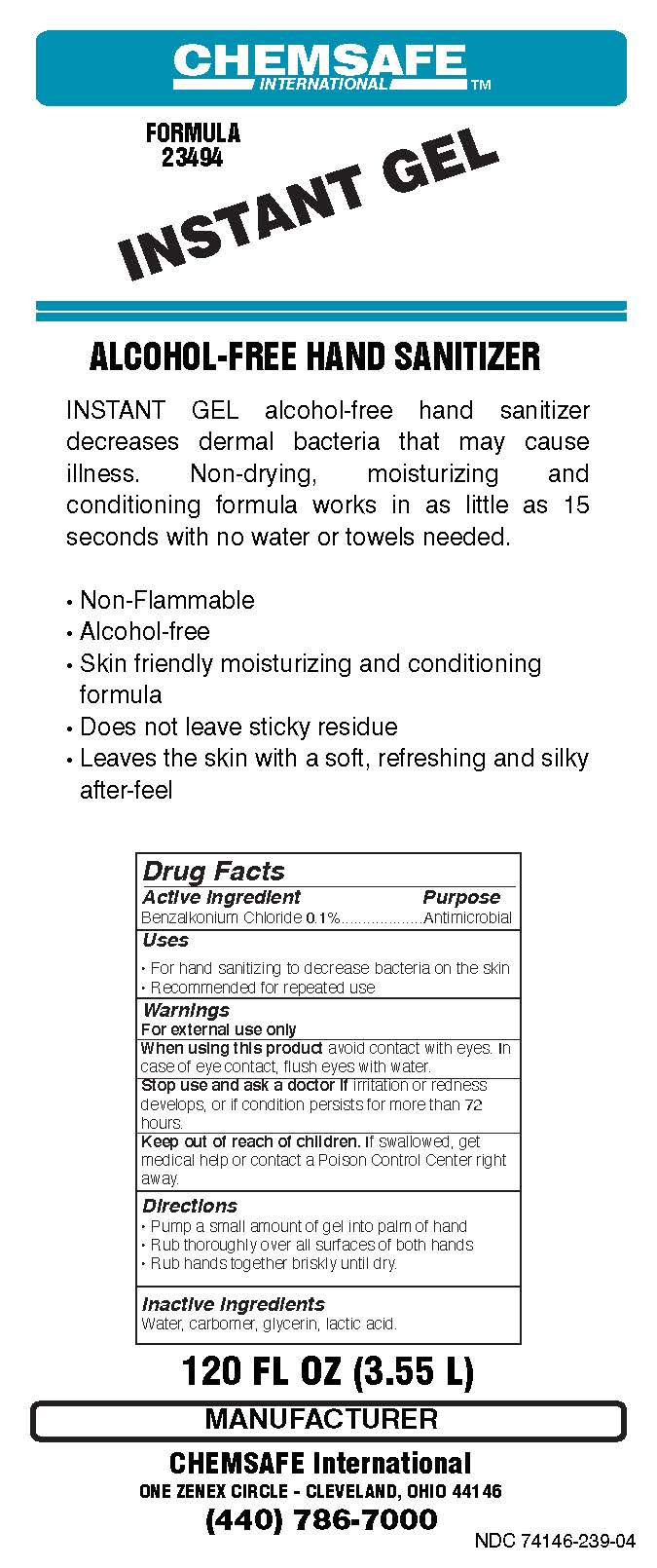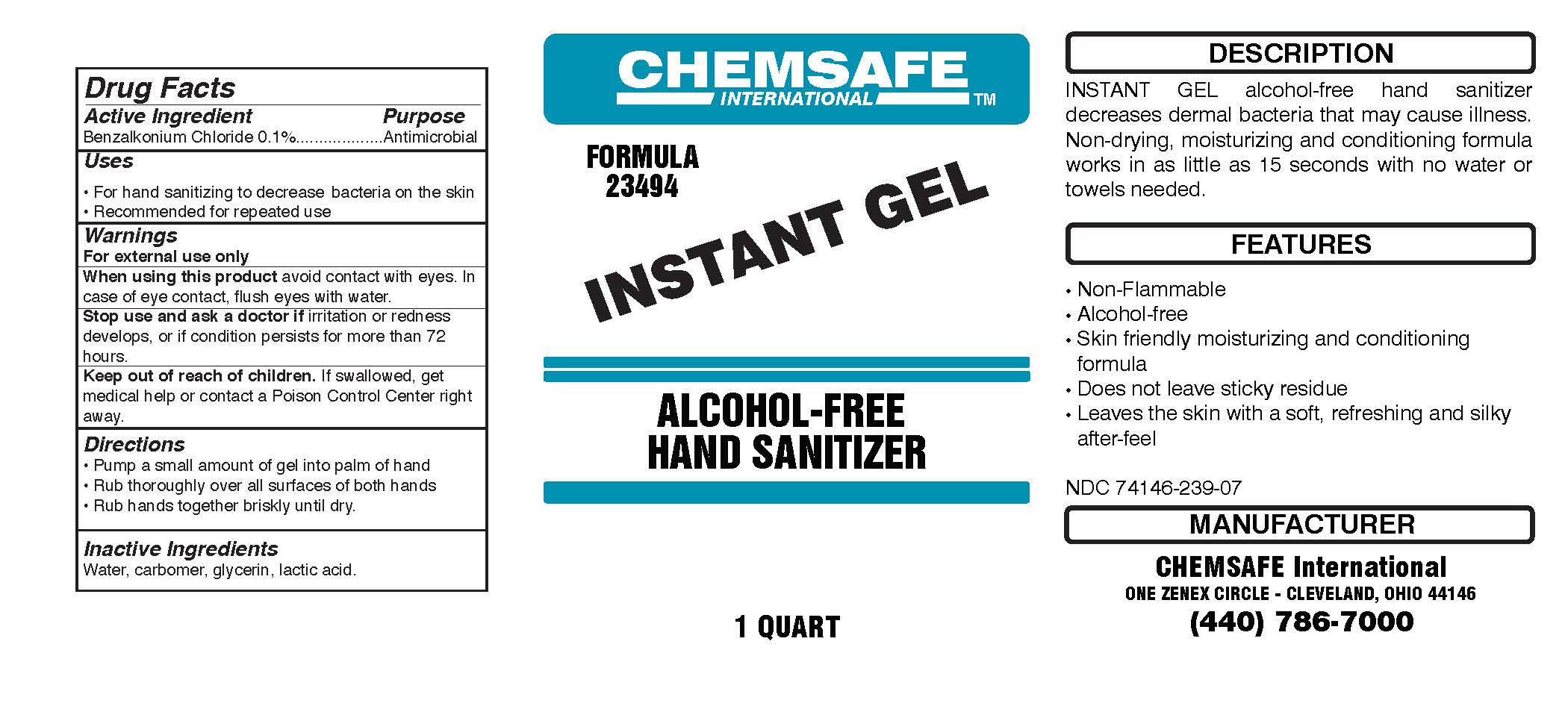 DRUG LABEL: Instant Gel
NDC: 74146-239 | Form: GEL
Manufacturer: GM Industrial, Inc.
Category: otc | Type: HUMAN OTC DRUG LABEL
Date: 20201210

ACTIVE INGREDIENTS: BENZALKONIUM CHLORIDE 1 mg/1 mL
INACTIVE INGREDIENTS: LACTIC ACID; WATER; GLYCERIN; CARBOMER HOMOPOLYMER, UNSPECIFIED TYPE

BOXED WARNING

ACTIVE INGREDIENT

Benzalkonium Chloride 0.1%

PURPOSE

Antimicrobial

INDICATIONS AND USAGE

- For hand sanitizing to decrease bacteria on the skin
- Recommended for repeated use

WARNINGS

For external use only

When using this product, avoid contact with eyes. In case of eye contact, flush eyes with water.

Stop use and ask a doctor if irritation or redness develops, or if condition persists for more than 72 hours.

Keep out of reach of children. If swallowed, get medical help or contact a Poison Control Center right away.

DOSAGE AND ADMINISTRATION

- Pump a small amount of gel into palm of hand
- Rub thoroughly over all surfaces of both hands
- Rub hands together briskly until dry.

INACTIVE INGREDIENT

Water, carbomer, glycerin, lactic acid.

PACKAGE LABEL

1 Gal 74146-239-01

PACKAGE LABEL

1 Gal NDC 74146-239-10

PACKAGE LABEL

1000 mL NDC 74146-239-02

PACKAGE LABEL

1000 mL NDC: 74146-239-11

PACKAGE LABEL

2.5 L NDC 74146-239-03

PACKAGE LABEL

2.5 L NDC 74146-239-12

PACKAGE LABEL

3.55 L NDC: 74146-239-04

PACKAGE LABEL

3.55 NDC 74146-239-13

PACKAGE LABEL

100 mL NDC 74146-239-05

PACKAGE LABEL

100 mL NDC 74146-239-14

PACKAGE LABEL

200 mL NDC 74146-239-06

PACKAGE LABEL

200 mL NDC 74146-239-15

PACKAGE LABEL

1 QT 74146-239-07

PACKAGE LABEL

1 QT NDC 74146-239-16